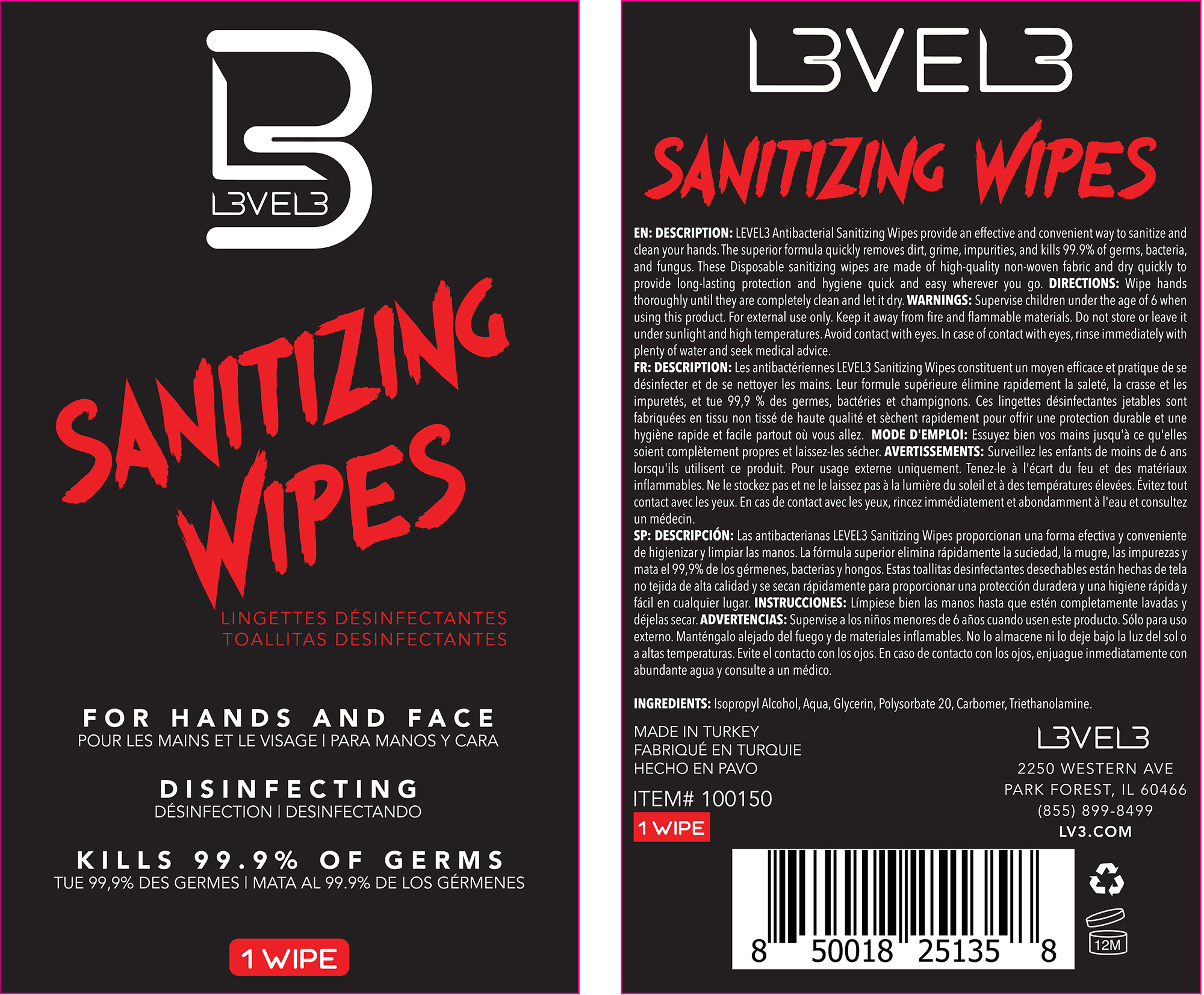 DRUG LABEL: Sanitizing Wipe
NDC: 80848-005 | Form: CLOTH
Manufacturer: L3VEL3 LLC
Category: otc | Type: HUMAN OTC DRUG LABEL
Date: 20201016

ACTIVE INGREDIENTS: ISOPROPYL ALCOHOL 70 mL/100 mL
INACTIVE INGREDIENTS: GLYCERIN 1 mL/100 mL; TROLAMINE; WATER; POLYSORBATE 20 1 mL/100 mL

Sanitizing Wipes

Purpose

Sanitizing Wipe

Description

LEVEL3 antibacterial hand wipes provide an effective and convenient way to sanitize and clean your hands. The superior formula quickly removes dirt, grime, impurities, and kills 99.9% of germs, bacteria, and fungus. These Disposable sanitizing wipes are made of high-quality non-woven fabric and dry quickly to provide long-lasting protection and hygiene quick and easy wherever you go.

Directions

Wipe hands thoroughly until they are completely clean and let it dry

Warnings

Supervise children under the age of 6 when using this product. For external use only. Keep it away from fire and flammable materials. Do not store or leave it under sunlight and high temperatures. Avoid contact with eyes. In case of contact with eyes, rinse immediately with plenty of water and seek medical advice.

KEEP OUT OF REACH OF CHILDREN

Supervise children under the age of 6 when using this product.

Active Ingredient(s)

Isopropyl Alcohol

Inactive ingredients

Aqua, Glycerine, Polysorbate 20, Carbomer, Triethanolamine.

Package Label - Principal Display Panel

1pk NDC: 80848-005-01